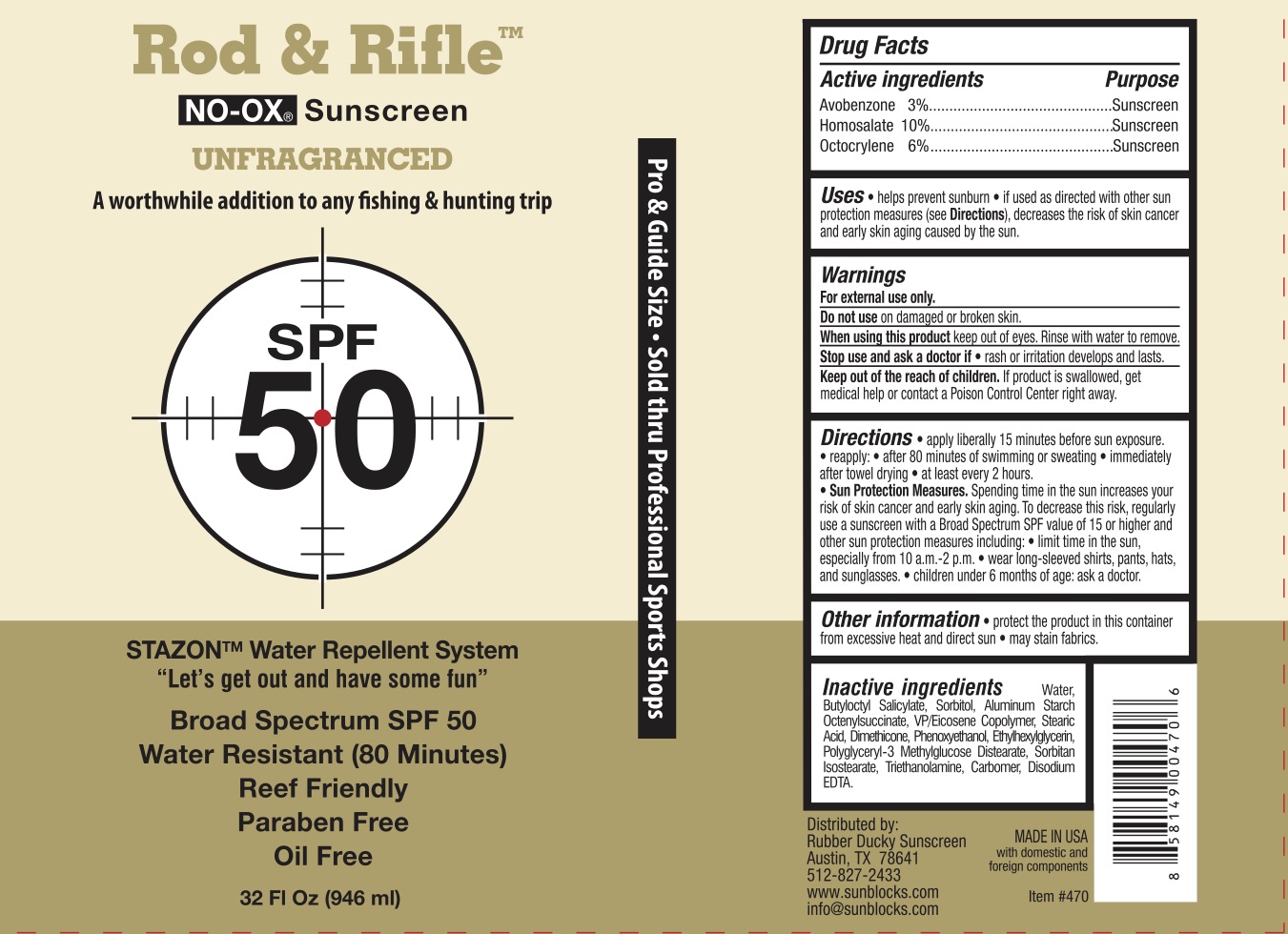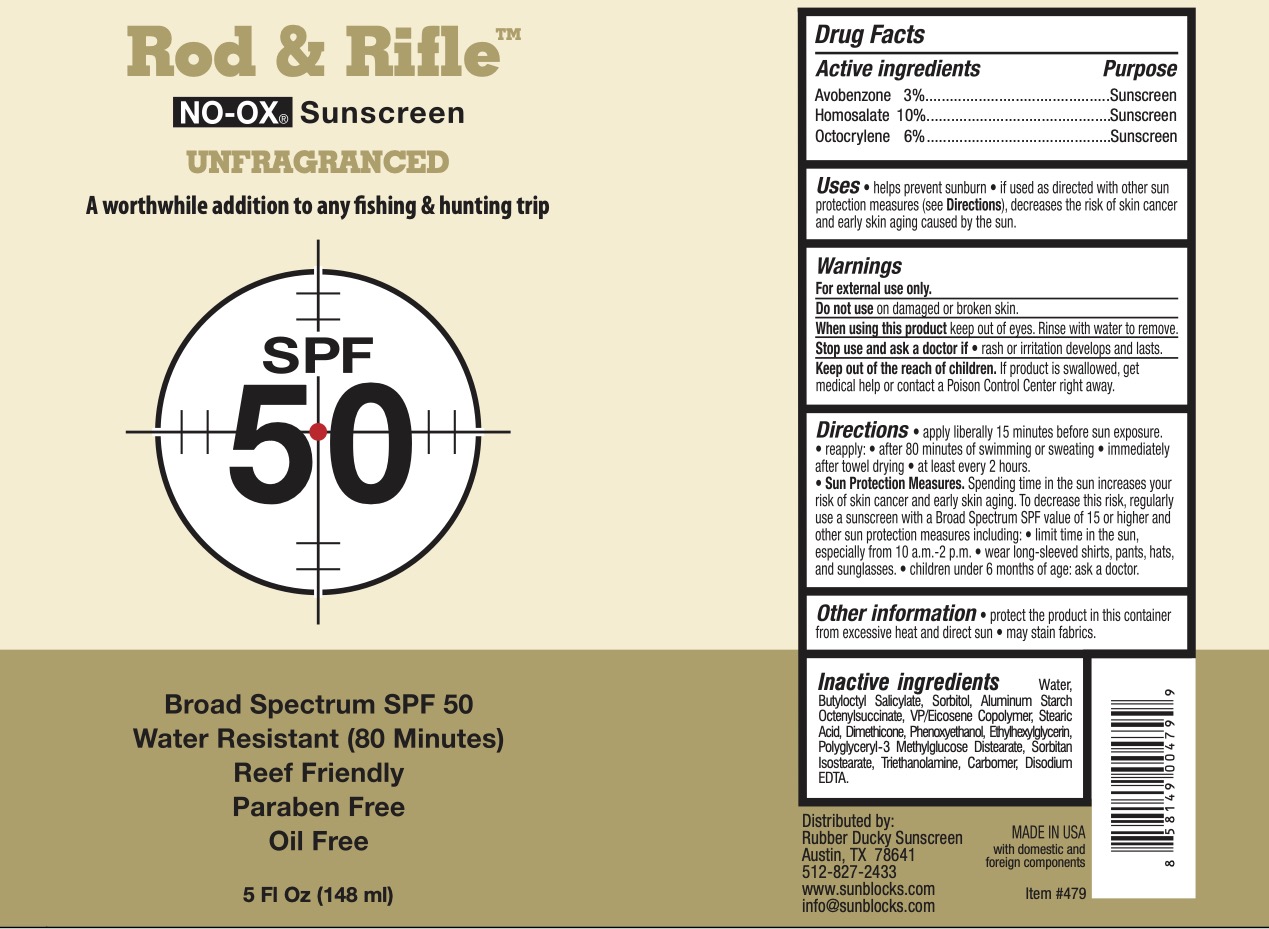 DRUG LABEL: Rod and Rifle SPF 50 Sunscreen
NDC: 72839-247 | Form: LOTION
Manufacturer: Derma Care Research Labs, LLC
Category: otc | Type: HUMAN OTC DRUG LABEL
Date: 20241219

ACTIVE INGREDIENTS: AVOBENZONE 3 g/100 mL; OCTOCRYLENE 6 g/100 mL; HOMOSALATE 10 g/100 mL
INACTIVE INGREDIENTS: SORBITOL; TROLAMINE; EDETATE DISODIUM; EICOSYL POVIDONE; ALUMINUM STARCH OCTENYLSUCCINATE; ETHYLHEXYLGLYCERIN; PHENOXYETHANOL; POLYGLYCERYL-3 DISTEARATE; SORBITAN ISOSTEARATE; STEARIC ACID; WATER; DIMETHICONE 200; BUTYLOCTYL SALICYLATE; CARBOMER 940

Rod and Rifle SPF 50 Sunscreen Lotion

Active Ingredients

Avobenzone 3%, Homosalate 10%, Octocrylene 6%

Purpose

Sunscreen

Uses

Helps prevent sunburn. If used as directed with other sun protection measures (see Directions), decreases the risk of skin cancer and early skin aging caused by the sun.

Warnings

For external use only.

Do not use on damaged or broken skin. When using this product keep out of eyes. Rinse eyes with water to remove.

Stop use and ask a doctor if rash occurs.

Keep Out of Reach of Children.

If swallowed, get medical help or contact a Poison Control Center right away.

Directions

Apply liberally 15 minutes before sun exposure. Reapply:

- after 80 minutes of swimming or sweating
- immediately after towel drying
- at least every 2 hours

Sun protection measures: spending time n the sun increases your risk of skin cancer and early skin aging. To decrease risk, regularly use a sunscreen with broad spectrum SPF of 15 or higher and other sun protection measure including:

- limit time in the sun, especially from 10 am to 2 pm
- wear long-sleeved shirts, pants, hats, and sunglasses.
- Children under 6 months: ask a doctor.

Inactive Ingredients

Water, Butyloctyl Salicylate, Sorbitol, Aluminum Starch Octenylsuccinate, VP/Eicosene Copolymer, Stearic Acid, Dimethicone, Phenoxyethanol, Ethylhexylglycerin, Polyglyceryl-3 Methylglucose Distearate, Sorbitan Isostearate, Triethanolamine, Carbomer, Disodium EDTA.